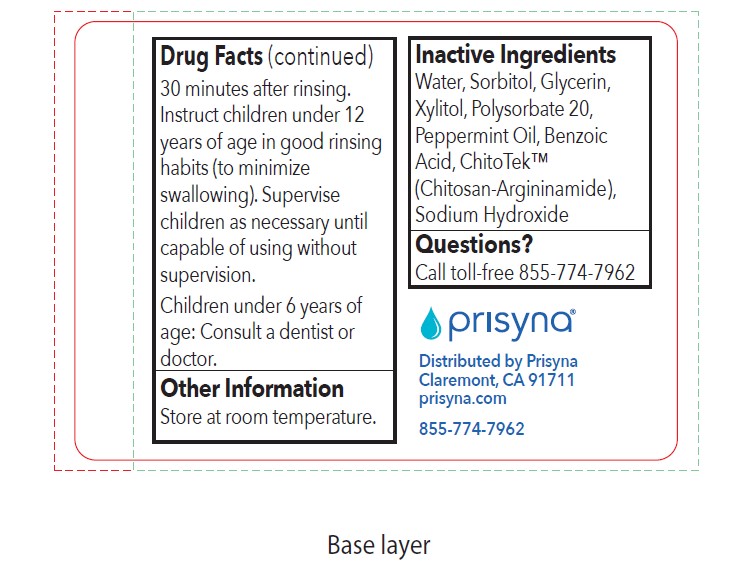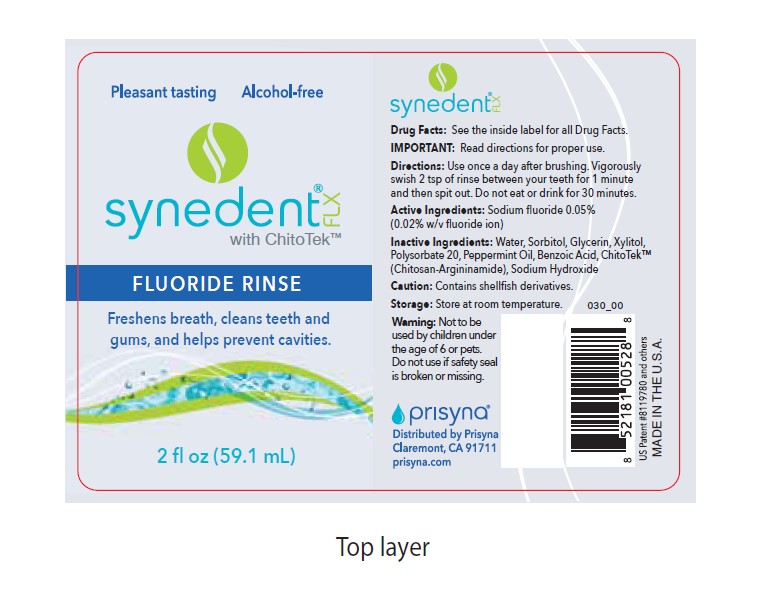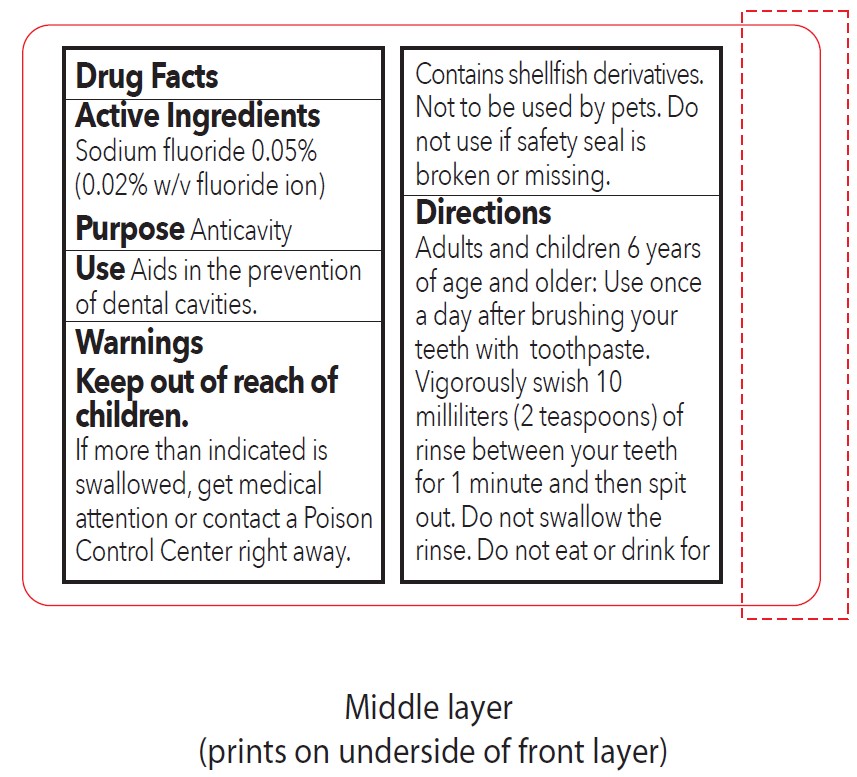 DRUG LABEL: Synedent FLX
NDC: 42368-005 | Form: MOUTHWASH
Manufacturer: Synedgen Inc.
Category: otc | Type: HUMAN OTC DRUG LABEL
Date: 20200305

ACTIVE INGREDIENTS: SODIUM FLUORIDE 0.02 g/100 mL
INACTIVE INGREDIENTS: WATER 49.882 g/100 mL

Synedent FLX 2 oz

Drug Facts

Active Ingredients

Sodium fluoride 0.05% (0.02% fluoride ion)

Purpose Anticavity

Use Aids in the prevention of dental cavities

Warnings

Keep out of reach of children.

If more than indicated is swallowed, get medical attention or contact a Poison Control Center right away. Contains shellfish derivatives. Not to be used by pets. Do not use if safety seal is broken or missing.

Directions

Adults and children 6 years of age and older: Use once a day after brushing your teeth with toothpaste. Vigorously swish 10 milliliters (2 teaspoons) of rinse between your teeth for 1 minute and then spit out. Do not swallow the rinse. Do not eat or drink for 30 minutes after rinsing. Instruct children under 12 years of age in good rinsing habits (to minimize swallowing). Supervise children as necessary until capable of using without supervision.

Children under 6 years of age: Consult a dentist or doctor.

Other Information

Store at room temperature.

Inactive Ingredients

Water, Sorbitol, Glycerin, Xylitol, Polysorbate 20, Peppermint Oil, Benzoic Acid, ChitoTek (Chitosan Argininamide), Sodium Hydroxide

Question?

Call toll-free 855-774-7962

Active Ingredients

Sodium fluoride 0.05%

(0.02% w/v fluoride ion)

Keep out of reach of children

Warnings

If more than indicates is swallowed, get medical attention or contact Poison Control Center right away.

Contains shellfish derivatives.

Not to be used by pets.

Do not use if safety seal is broken or missing.

Directions

Adults and children 6 years of age and older: Use once a day after brushing your teeth with toothpaste. Vigorously swish 10 milliliters (2 teaspoons) of rinse between your teeth for 1 minute and then spit out. Do not swallow the rinse. Do not eat or drink for 30 minutes after rinsing. Instruct children under 12 years of age in good rinsing habits (to minimize swallowing). Supervise children as necessary until capable of using without supervision.

Inactive Ingredients

Water, Sorbitol, Glycerin, Xylitol, Polysorbate 20, Peppermint Oil, Benzoic Acid, ChitoTek (Chitosan Argininamide), Sodium Hydroxide

Purpose

Anticavity

Use

Aids in the prevention of dental cavities